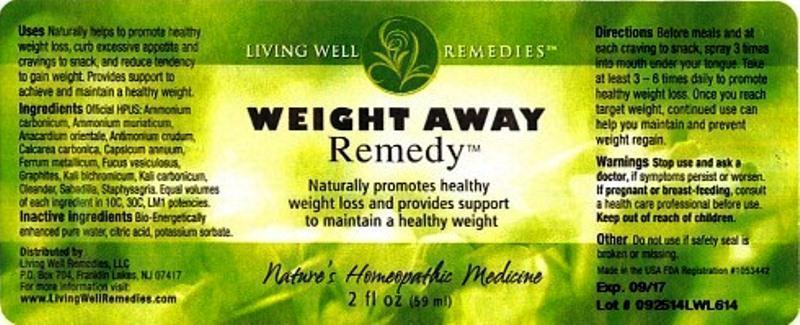 DRUG LABEL: Weight Away Remedy
NDC: 53852-0006 | Form: LIQUID
Manufacturer: Living Well Remedies, LLC
Category: homeopathic | Type: HUMAN OTC DRUG LABEL
Date: 20141030

ACTIVE INGREDIENTS: POTASSIUM DICHROMATE 10 [hp_C]/59 mL; OYSTER SHELL CALCIUM CARBONATE, CRUDE 10 [hp_C]/59 mL; ANTIMONY TRISULFIDE 10 [hp_C]/59 mL; CAPSICUM 10 [hp_C]/59 mL; SCHOENOCAULON OFFICINALE SEED 10 [hp_C]/59 mL; FUCUS VESICULOSUS 10 [hp_C]/59 mL; GRAPHITE 10 [hp_C]/59 mL; AMMONIUM CHLORIDE 10 [hp_C]/59 mL; SEMECARPUS ANACARDIUM JUICE 10 [hp_C]/59 mL; NERIUM OLEANDER LEAF 10 [hp_C]/59 mL; POTASSIUM CARBONATE 10 [hp_C]/59 mL; DELPHINIUM STAPHISAGRIA SEED 10 [hp_C]/59 mL; AMMONIUM CARBONATE 10 [hp_C]/59 mL; IRON 10 [hp_C]/59 mL
INACTIVE INGREDIENTS: WATER; CITRIC ACID MONOHYDRATE; POTASSIUM SORBATE

Weight Away Remedy

DOSAGE AND ADMINISTRATION

Directions: Before meals and at each craving to snack, spray 3 times into mouth. Take at least 3 - 6 times daily to promote healthy weight loss. To maximize results, also spray Weight Remedy 3 times daily directly onto the skin on target areas of your body where you are trying to lose weight. Continued use can help you maintain a healthy weight and prevent weight regain.

WARNINGS

Warnings: Stop use and ask a doctor, if symptoms persist or worsen. If pregnant or breast-feeding, consult a healthcare professional before use.

Keep out of reach of children.

OTHER SAFETY INFORMATION

Other: Do not use if safety seal is broken or missing.

PURPOSE

Uses: Naturally helps to promote healthy weight loss, curb excessive appetite and cravings to snack, and reduce tendency to gain weight. Provides support to achieve and maintain a healthy weight.

ACTIVE INGREDIENT

Ingredients: Official HPUS: Kali bichromicum, Calcarea carbonica, Antimonium crudum, Capsicum annuu, Sabadilla, Fucus vesiculosus, Graphites, Ammonium muriaticum, Anacardium orientale, Oleander, Kali carbonicum, Staphysagria, Ammonium carbonicum, Ferrum metallicum. Equal volumes of each ingredient in 10C, 30C, LM1 potencies.

INACTIVE INGREDIENT

Inactive ingredients: Bio-Energetically enhanced pure water, citric acid, potassium sorbate.

INDICATIONS AND USAGE

Uses: Naturally helps to promote healthy weight loss, curb excessive appetite and cravings to snack, and reduce tendency to gain weight. Provides support to achieve and maintain a healthy weight.